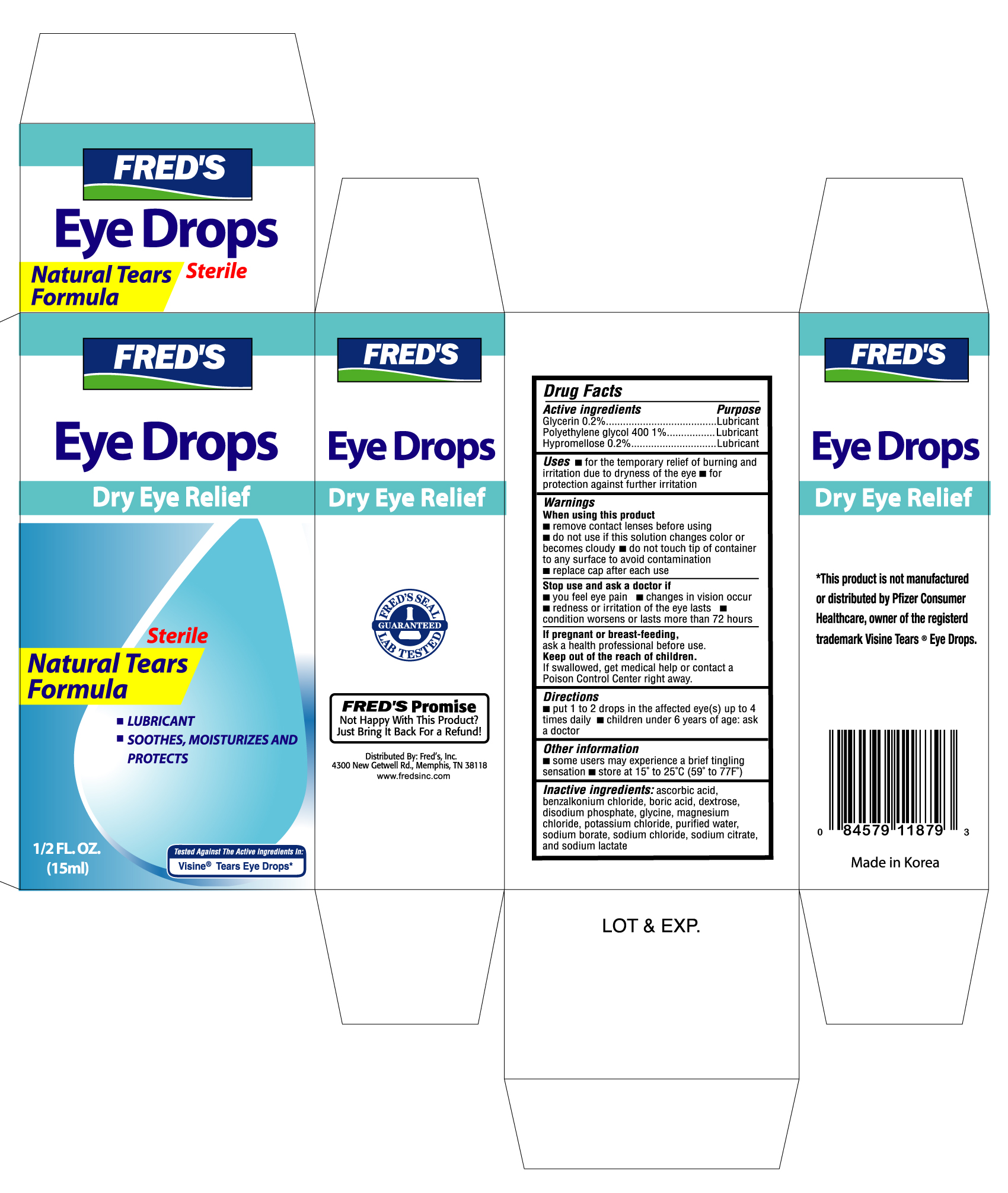 DRUG LABEL: FREDS DRY EYE RELIEF
NDC: 11716-1189 | Form: SOLUTION
Manufacturer: HANLIM PHARM. CO., LTD.
Category: otc | Type: HUMAN OTC DRUG LABEL
Date: 20101206

ACTIVE INGREDIENTS: GLYCERIN 0.002 mL/1 mL; POLYETHYLENE GLYCOL 400 0.01 mL/1 mL; HYPROMELLOSES 0.002 mL/1 mL
INACTIVE INGREDIENTS: ASCORBIC ACID; BENZALKONIUM CHLORIDE; BORIC ACID; DEXTROSE; GLYCINE; MAGNESIUM CHLORIDE; POTASSIUM CHLORIDE; WATER; SODIUM BORATE; SODIUM CHLORIDE; SODIUM CITRATE; SODIUM LACTATE

Drug Facts

Active ingredients Purpose

Glycerin 0.2% ....................................................................Lubricant

Polyethylene Glycol 400 1% ...............................................Lubricant

Hypromellose 0.2% ............................................................Lubricant

Uses

- for the temporary relief of burning and irritation due to dryness of the eye
- for protection against further irritation

Warnings

For external use only

When using this product

- remove contact lenses before using
- do not use if this solution changes color or becomes cloudy
- do not touch tip of container to any surface to avoid contamination
- replace cap after each use

Stop use and ask a doctor if

- you feel eye pain
- changes in vision occur
- redness or irritation of the eye lasts
- condition worsens or lasts more than 72 hours

If pregnant or breast-feeding,

ask a health professional before use.

Keep out of the reach of children.

If swallowed, get medical help or contact a Poison Control Center right away.

Directions

- put 1 to 2 drops in the affected eye(s) up to 4 times daily
- children under 6 years of age: ask a doctor

Other information

- some users may experience a brief tingling sensation
- store at 15o to 25oC (59o to 77oF)

INACTIVE INGREDIENT

Inactive ingredients: ascorbic acid, benzalkonium chloride, boric acid, dextrose, disodium phosphate, glycine, magnesium chloride, potassium chloride, purified water,

sodium borate, sodium chloride, sodium citrate, and sodium lactate

DOSAGE AND ADMINISTRATION

Distributed by: Fred's Inc.

4300 New Getwell Rd.

Memphis, TN 38118

www.fredsinc.com

PACKAGE LABEL

Enter section text here